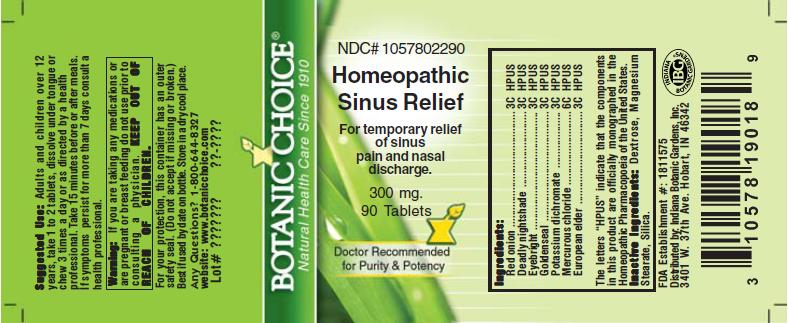 DRUG LABEL: Homeopathic Sinus Relief Formula
NDC: 10578-022 | Form: TABLET
Manufacturer: Indiana Botanic Gardens
Category: homeopathic | Type: HUMAN OTC DRUG LABEL
Date: 20110624

ACTIVE INGREDIENTS: ONION 3 [hp_C]/1 1; ATROPA BELLADONNA 3 [hp_C]/1 1; EUPHRASIA STRICTA 3 [hp_C]/1 1; GOLDENSEAL 3 [hp_C]/1 1; POTASSIUM DICHROMATE 3 [hp_C]/1 1; SAMBUCUS NIGRA FLOWERING TOP 3 [hp_C]/1 1; CALOMEL 6 [hp_C]/1 1
INACTIVE INGREDIENTS: DEXTROSE; MAGNESIUM STEARATE ; SILICON DIOXIDE 

Homeopathic Sinus Relief Formula

ACTIVE INGREDIENT

I n g r e d i e n t s :

Red onion............................... 3C HPUS
Deadly nightshade................................ 3C HPUS
Eyebright.................... 3C HPUS
Goldenseal................. 3C HPUS
Potassium dichromate.......................... 3C HPUS
Mercurous chloride......................... 6C HPUS
European elder........................ 3C HPUS

The letters “HPUS” indicate that the components in
this product are officially monographed in the
Homeopathic Pharmacopoeia of the United States.

PURPOSE

For temporary relief of sinus pain and nasal discharge

KEEP OUT OF
REACH OF CHILDREN.

INDICATIONS AND USAGE

For temporary relief of sinus pain and nasal discharge

WARNINGS

Warning: If you are taking any medications or
are pregnant or breast feeding do not use prior to
consulting a physician.

DOSAGE AND ADMINISTRATION

Suggested Use: Adults and children over 12
years, take 1-2 tablets, dissolve under tongue or
chew 3 times a day or as directed by a health care
professional. Take 15 minutes before or after meals.
If symptoms persist for more than 7 days consult a
health professional.

Inactive Ingredients: Dextrose, Magnesium
Stearate, Silica.

PACKAGE LABEL

NDC# 1057802290

Homeopathic Sinus Relief Formula

For temporary relief of sinus pain and nasal discharge

300 mg.
90 Tablets

USER SAFETY WARNINGS

For your protection, this container has an outer
safety seal. (Do not accept if missing or broken.)
Best if used by date on bottle. Store in a dry cool place.
Any Questions? 1-800-644-8327
website: www.botanicchoice.com

FDA Establishment #: 1811575

Distributed by: Indiana Botanic Gardens, Inc.
3401 W. 37th Ave. Hobart, IN 46342